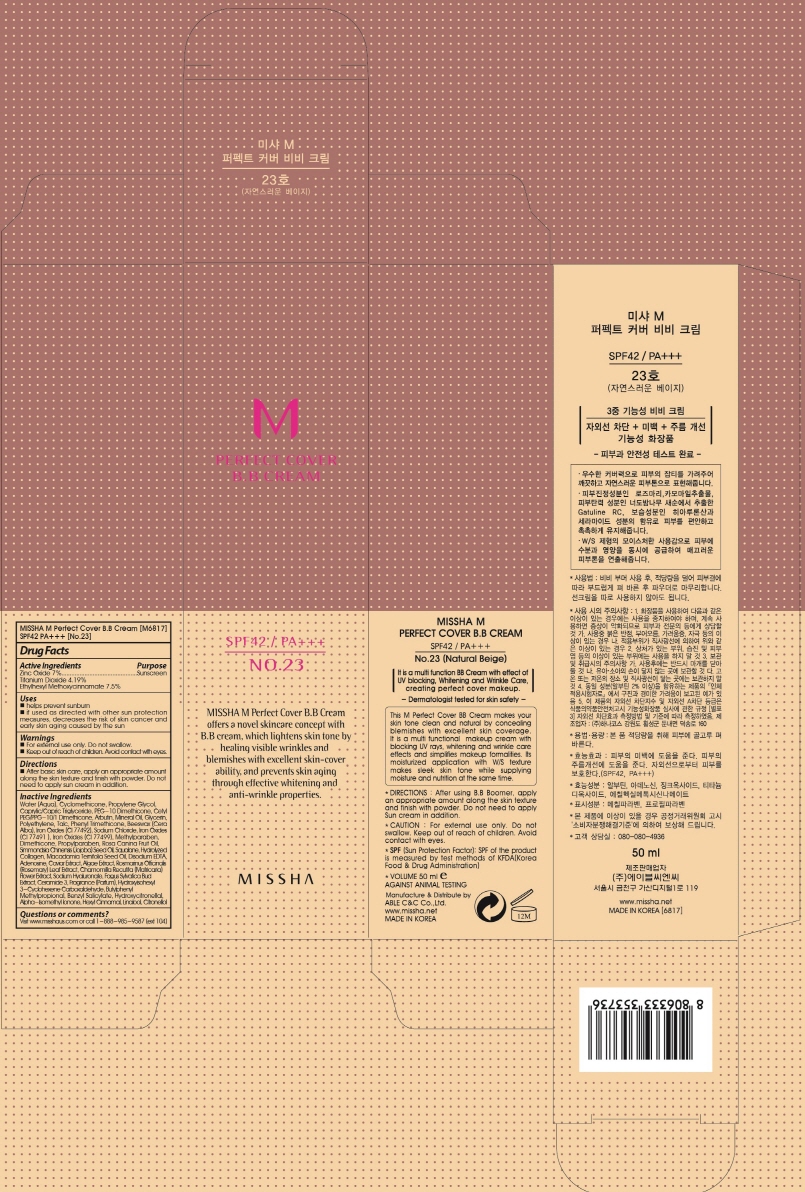 DRUG LABEL: MISSHA M Perfect Cover BB No 23
NDC: 13733-160 | Form: CREAM
Manufacturer: Able C&C Co., Ltd.
Category: otc | Type: HUMAN OTC DRUG LABEL
Date: 20241204

ACTIVE INGREDIENTS: ZINC OXIDE 3.5 g/50 mL; TITANIUM DIOXIDE 2.09 g/50 mL; OCTINOXATE 3.75 g/50 mL
INACTIVE INGREDIENTS: PEG-10 DIMETHICONE (600 CST); FERRIC OXIDE YELLOW; SODIUM CHLORIDE; FERROSOFERRIC OXIDE; SQUALANE; TRIS(TRIMETHYLSILOXY)PHENYLSILANE; FERRIC OXIDE RED; METHYLPARABEN; PROPYLPARABEN; CYCLOMETHICONE 4; LAMINARIA HYPERBOREA; FAGUS SYLVATICA FLOWER BUD; BENZOIC ACID; HYALURONATE SODIUM; MACADAMIA OIL; EDETATE DISODIUM ANHYDROUS; ROSEMARY; BUTYLENE GLYCOL; PHENOXYETHANOL; TROPOLONE; WATER; CYCLOMETHICONE; PROPYLENE GLYCOL; MEDIUM-CHAIN TRIGLYCERIDES; GLYCERIN; MINERAL OIL; HIGH DENSITY POLYETHYLENE; YELLOW WAX; JOJOBA OIL; CERAMIDE AP; CAPRYLHYDROXAMIC ACID; ABRONIA VILLOSA LEAF; ARBUTIN; TALC; DIMETHICONE; ADENOSINE; CHAMOMILE FLOWER OIL; CAPRYLYL GLYCOL; BENZYL ALCOHOL; 1,2-HEXANEDIOL

MISSHA M Perfect Cover BB No 23

Active Ingredient

Active Ingredients: Zinc Oxide 7%, Titanium Dioxide 4.19%, Ethylhexyl Methoxycinnamate 7.5%

Purpose

Sunscreen

Uses

helps prevent sunburn

if used as directed with other sun protection measures (see Directions), decreases the risk of skin cancer and early skin aging caused by the sun

Directions

- apply liberally 15 minutes before sun exposure
- reapply at least every 2 hours
- use a water-resistant sunscreen if swimming or sweating

Sun protection Measures.Spending time in the sun increases your risk of skin cancer and early skin aging. To decrease this risk, regulary use a sunscreen with SPF value of 15 or higher and other sun protection measures including:

- limit time in the sun, especially from 10 a.m. - 2 p.m.
- wear long-sleeved shirts, pants, hats and sunglasses

Other Information

protect the product in this container from excessive heat and direct sun.

Questions or comments?

visit www.misshaus.com or call 1-888-985-9887(Ext 104)

Inactive Ingredients

Inactive Ingredients: Water (Aqua), Cyclomethicone, Propylene Glycol, Caprylic/Capric Triglyceride, PEG-10 Dimethicone, Cetyl PEG/PPG-10/1 Dimethicone, Arbutin, Mineral Oil, Glycerin, Polyethylene, Talc, Phenyl Trimethicone, Beeswax (Cera Alba), Iron Oxides (CI 77492), Sodium Chloride, Iron Oxides (CI 77491), Iron Oxides (CI 77499), Methylparaben, Dimethicone, Propylparaben, Rosa Canina Fruit Oil, Simmondsia Chinensis (Jojoba) Seed Oil, Squalane, Hydrolyzed Collagen, Macadamia Ternifolia Seed Oil, Disodium EDTA, Adenosine, Caviar Extract, Algae Extract, Rosmarinus Officinalis (Rosemary) Leaf Extract, Chamomilla Recutita (Matricaria) Flower Extract, Sodium Hyaluronate, Fagus Sylvatica Bud Extract, Ceramide 3, Fragrance (Parfum), Hydroxyisohexyl 3-Cyclohexene Carboxaldehyde, Butylphenyl Methylpropional, Benzyl Salicylate, Hydroxycitronellal, Alpha-Isomethyl Ionone, Hexyl Cinnamal, Linalool, Citronellol

Warnings:
Do not use on damaged or broken skin.
When using this product, keep out of eyes. Rinse with water to Remove.
Stop use and ask a doctor, if rash ocurs.

Keep out of reach of children.